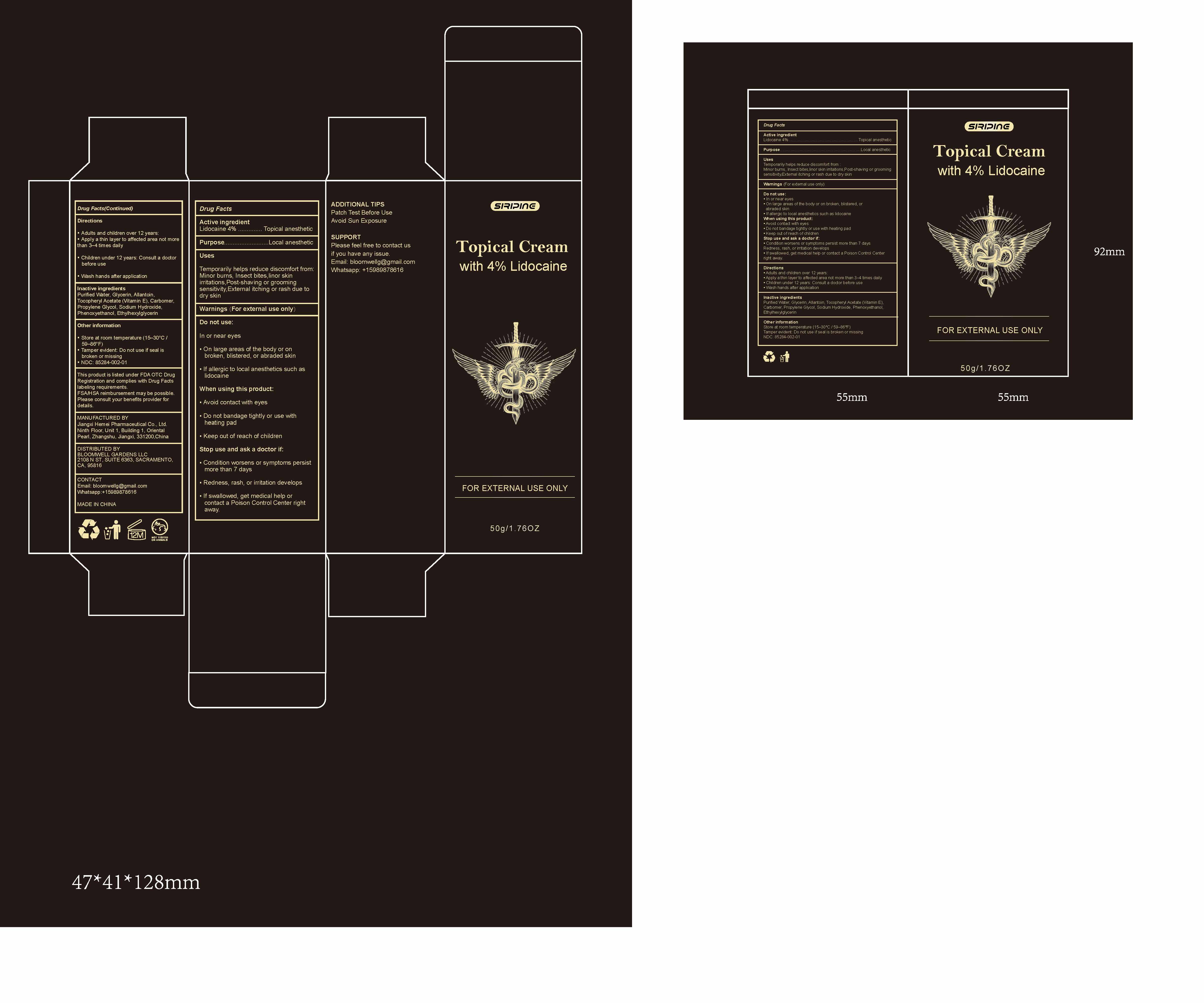 DRUG LABEL: Topical Cream
NDC: 85284-002 | Form: CREAM
Manufacturer: BLOOMWELL GARDENS LLC
Category: otc | Type: HUMAN OTC DRUG LABEL
Date: 20250616

ACTIVE INGREDIENTS: LIDOCAINE 4 g/100 g
INACTIVE INGREDIENTS: GLYCERIN; WATER; ETHYLHEXYLGLYCERIN; PHENOXYETHANOL; ALPHA-TOCOPHEROL ACETATE; ALLANTOIN; CARBOMER; PROPYLENE GLYCOL; SODIUM HYDROXIDE

ACTIVE INGREDIENT

Lidocaine 4% ---Topical anesthetic

PURPOSE

Local anesthetic

Uses

Temporarily helps reduce discomfort from :

Minor burns, Insect bites,linor skin irritations,Post-shaving or grooming

sensitivity,External itching or rash due to dry skin

Warnings

For external use only

Do not use:

In or near eyes

▪ On large areas of the body or on broken, blistered, or abraded skin

▪ If allergic to local anesthetics such as lidocaine

When using this product:

▪ Avoid contact with eyes

▪ Do not bandage tightly or use with heating pad

▪ Keep out of reach of children

Stop use and ask a doctor if:

▪ Condition worsens or symptoms persist more than 7 days

Redness, rash, or irritation develops

▪ If swallowed, get medical help or contact a Poison Control Center right away.

Directions

▪ Adults and children over 12 years:

▪ Apply a thin layer to affected area not more than 3–4 times daily

▪ Children under 12 years: Consult a doctor before use

▪ Wash hands after application

Inactive ingredients

Purified Water, Glycerin, Allantoin, Tocopheryl Acetate (Vitamin E),

Carbomer, Propylene Glycol, Sodium Hydroxide, Phenoxyethanol,

Ethylhexylglycerin

Other information

Store at room temperature (15–30°C / 59–86°F)

Tamper evident: Do not use if seal is broken or missing